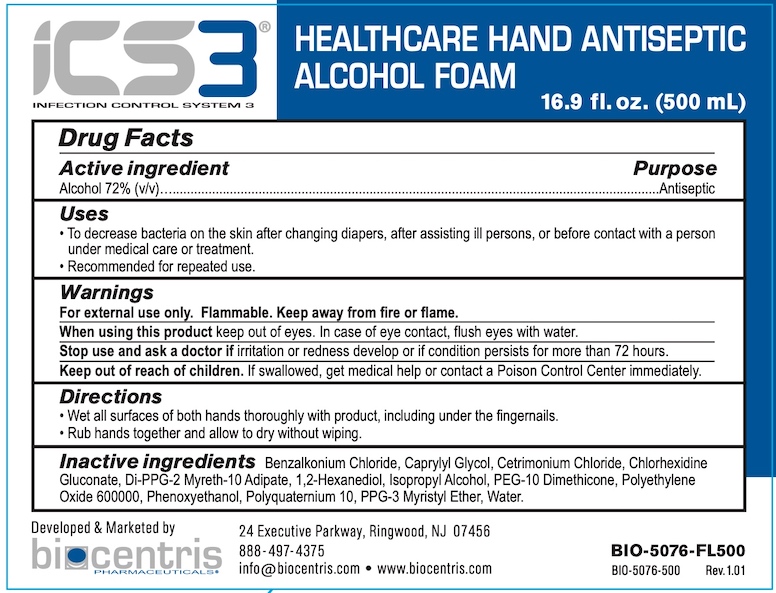 DRUG LABEL: ICS3 Blue Healthcare Hand Antiseptic
NDC: 81232-161 | Form: LIQUID
Manufacturer: Biocentris Pharmaceuticals, LLC
Category: otc | Type: HUMAN OTC DRUG LABEL
Date: 20210420

ACTIVE INGREDIENTS: ALCOHOL 72 mL/100 mL
INACTIVE INGREDIENTS: BENZALKONIUM CHLORIDE; CAPRYLYL GLYCOL; CETRIMONIUM CHLORIDE; CHLORHEXIDINE GLUCONATE; DI-PPG-2 MYRETH-10 ADIPATE; 1,2-HEXANEDIOL; ISOPROPYL ALCOHOL; PEG-10 DIMETHICONE (600 CST); POLYETHYLENE OXIDE 600000; PHENOXYETHANOL; POLYQUATERNIUM-10 (30000 MPA.S AT 2%); PPG-3 MYRISTYL ETHER; WATER

Biocentris ICS3 Blue Healthcare Hand Antiseptic

Drug Facts

Active ingredient

Alcohol 72% (v/v)

Purpose

Antiseptic

Uses

- To decrease bacteria on the skin after changing diapers, after assisting ill persons or before contact with a person under medical care or treatment.
- Recommended for repeated use.

Warnings

For external use only. Flammable. Keep away from fire or flame.

When using this product keep out of eyes. In case of eye contact, flush eyes with water.

Stop use and ask a doctor if irritation or redness develop or if condition persists for more than 72 hours.

Keep out of reach of children. If swallowed, get medical help or contact a Poison Control Center immediately.

Directions

- Wet all surfaces of both hands thoroughly with product, including under the fingernails.
- Rub hands together and allow to dry without wiping.

INACTIVE INGREDIENT

Inactive ingredients Benzalkonium Chloride, Caprylyl Gycol, Cetrimonium Chloride, Chlorhexidine Gluconate, Di-PPG-2 Myreth-10 Adipate, 1,2-Hexanediol, Isopropyl Alcohol, PEG-10 Dimethicone, Polyethylene Oxide 600000, Phenoxyethanol, Polyquaternium 10, PPG-3 Myristyl Ether, Water

Developed and Marketed by biocentris PHARMACEUTICALS

24 Executive Parkway, Ringwood, NJ 07456

888-497-4375

info@biocentris.com • www.biocentris.com

PACKAGE LABEL

ICS3®

INFECTION CONTROL SYSTEM 3

HEALTHCARE HAND ANTISEPTIC

ALCOHOL FOAM

16.9 FL OZ (500 mL)